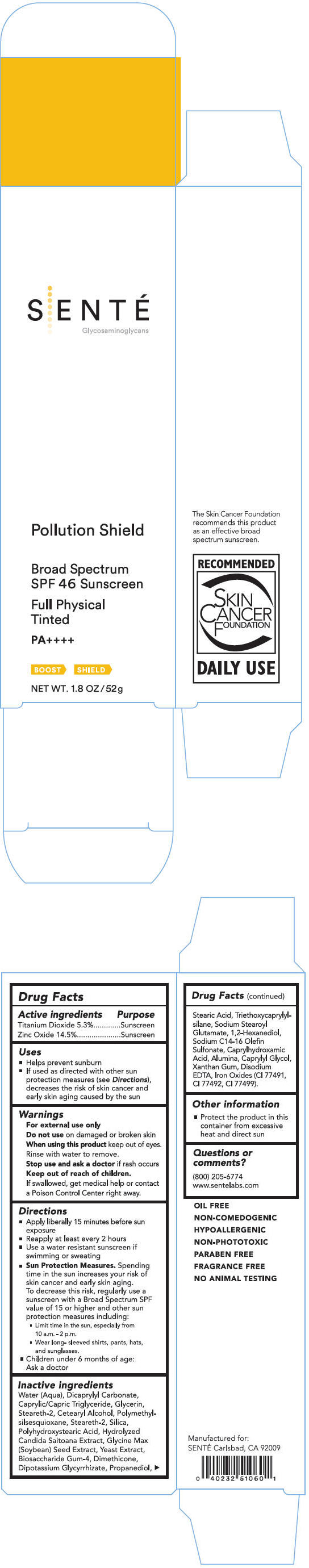 DRUG LABEL: Pollution Shield SPF 46 Broad Spectrum Sunscreen
NDC: 71398-001 | Form: LOTION
Manufacturer: SENTÉ, Inc.
Category: otc | Type: HUMAN OTC DRUG LABEL
Date: 20170512

ACTIVE INGREDIENTS: Titanium Dioxide 53 mg/1 g; Zinc Oxide 145 mg/1 g
INACTIVE INGREDIENTS: Dicaprylyl Carbonate; Medium-Chain Triglycerides; Glycerin; Steareth-2; Cetostearyl Alcohol; POLYMETHYLSILSESQUIOXANE (11 MICRONS); Steareth-21; Silicon Dioxide; POLYHYDROXYSTEARIC ACID (2300 MW); Soybean; Yeast, Unspecified; Biosaccharide Gum-4; Dimethicone; Glycyrrhizinate Dipotassium; Propanediol; Stearic Acid; Triethoxycaprylylsilane; Sodium Stearoyl Glutamate; 1,2-Hexanediol; Sodium C14-16 Olefin Sulfonate; Caprylhydroxamic Acid; Aluminum Oxide; Caprylyl Glycol; Xanthan Gum; Edetate Disodium; Ferrosoferric Oxide; Ferric Oxide Red; Ferric Oxide Yellow

Pollution Shield SPF 46 Broad Spectrum Sunscreen

Drug Facts

ACTIVE INGREDIENT

Active ingredients | Purpose
Titanium Dioxide 5.3% | Sunscreen
Zinc Oxide 14.5% | Sunscreen

Uses

- Helps prevent sunburn
- If used as directed with other sun protection measures (see Directions), decreases the risk of skin cancer and early skin aging caused by the sun

Warnings

For external use only

Do not use on damaged or broken skin

When using this product keep out of eyes. Rinse with water to remove.

Stop use and ask a doctor if rash occurs

Keep out of reach of children.

If swallowed, get medical help or contact a Poison Control Center right away.

Directions

- Apply liberally 15 minutes before sun exposure
- Reapply at least every 2 hours
- Use a water resistant sunscreen if swimming or sweating
- Sun Protection Measures. Spending time in the sun increases your risk of skin cancer and early skin aging. To decrease this risk, regularly use a sunscreen with a Broad Spectrum SPF value of 15 or higher and other sun protection measures including:
  - Limit time in the sun, especially from 10a.m.-2p.m.
  - Wear long- sleeved shirts, pants, hats, and sunglasses.
  - Children under 6 months of age: Ask a doctor

Inactive ingredients

Water (Aqua), Dicaprylyl Carbonate, Caprylic/Capric Triglyceride, Glycerin, Steareth-2, Cetearyl Alcohol, Polymethylsilsesquioxane, Steareth-21, Silica, Polyhydroxystearic Acid, Hydrolyzed Candida Saitoana Extract, Glycine Max (Soybean) Seed Extract, Yeast Extract, Biosaccharide Gum-4, Dimethicone, Dipotassium Glycyrrhizate, Propanediol, Stearic Acid, Triethoxycaprylylsilane, Sodium Stearoyl Glutamate, 1,2-Hexanediol, Sodium C14-16 Olefin Sulfonate, Caprylhydroxamic Acid, Alumina, Caprylyl Glycol, Xanthan Gum, Disodium EDTA. Iron Oxides (Cl 77491, Cl 77492, Cl 77499).

Other information

- Protect the product in this container from excessive heat and direct sun

Questions or comments?

(800) 205-6774

www.sentelabs.com

PRINCIPAL DISPLAY PANEL - 52 g Tube Carton

SENTÉ
Glycosaminoglycans

Pollution Shield

Broad Spectrum
SPF 46 Sunscreen

Full Physical
Tinted

PA++++

BOOST
SHIELD

NET WT. 1.8 OZ/52g